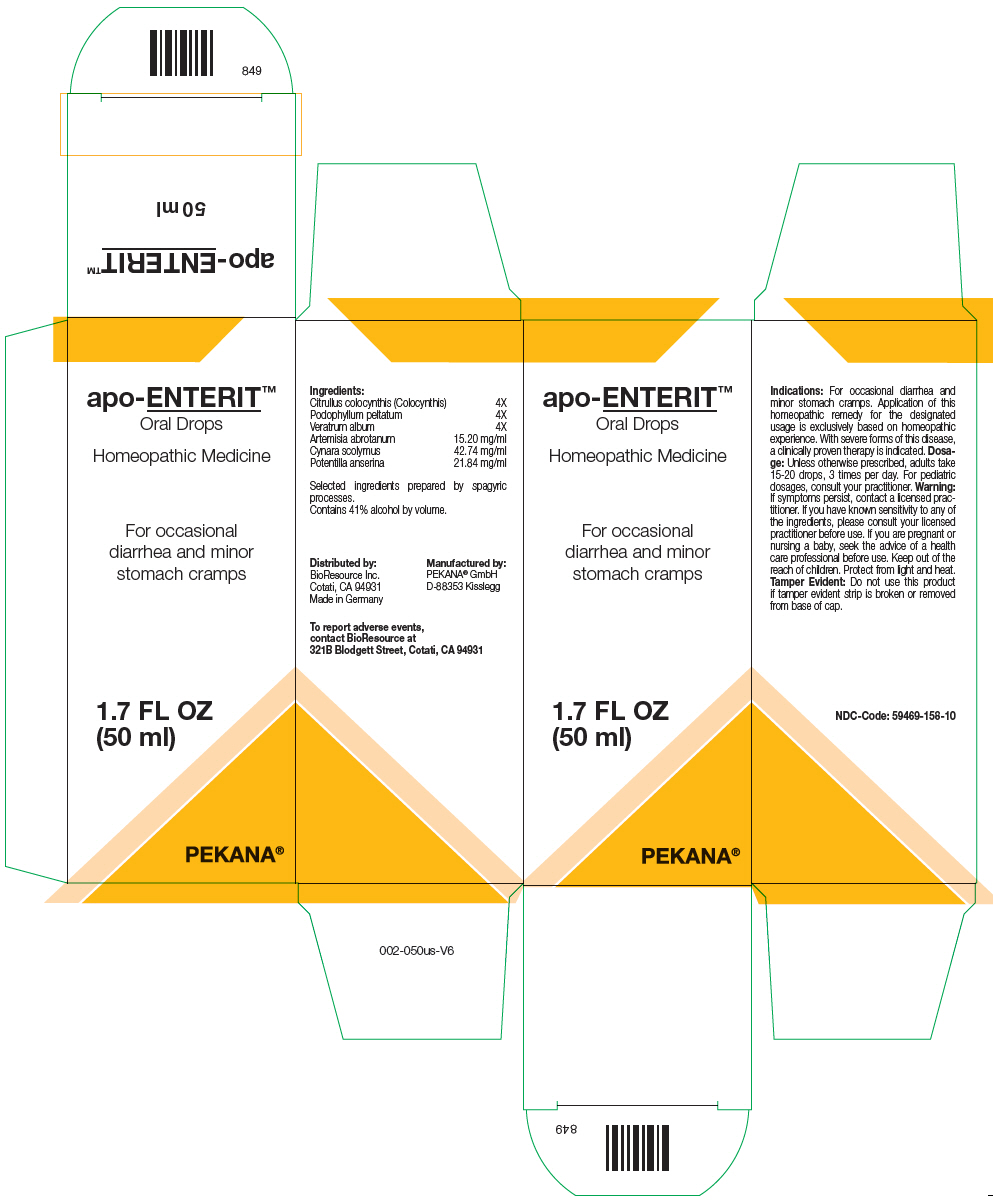 DRUG LABEL: apo-ENTERIT
NDC: 59469-158 | Form: SOLUTION/ DROPS
Manufacturer: PEKANA Naturheilmittel GmbH
Category: homeopathic | Type: HUMAN OTC DRUG LABEL
Date: 20221202

ACTIVE INGREDIENTS: Citrullus colocynthis Fruit Pulp 4 [hp_X]/50 mL; Podophyllum 4 [hp_X]/50 mL; Veratrum album Root 4 [hp_X]/50 mL; Artemisia abrotanum Flowering Top 760 mg/50 mL; Cynara scolymus Whole 2137 mg/50 mL; Potentilla anserina Flowering Top 1092 mg/50 mL
INACTIVE INGREDIENTS: Water; Alcohol

apo-ENTERIT™

ACTIVE INGREDIENT

Ingredients:
Citrullus colocynthis (Colocynthis) | 4X
Podophyllum peltatum | 4X
Veratrum album | 4X
Artemisia abrotanum | 15.20 mg/ml
Cynara scolymus | 42.74 mg/ml
Potentilla anserina | 21.84 mg/ml

Selected ingredients prepared by spagyric processes.

INACTIVE INGREDIENT

Contains 41% alcohol by volume.

Indications

PURPOSE

For occasional diarrhea and minor stomach cramps. Application of this homeopathic remedy for the designated usage is exclusively based on homeopathic experience. With severe forms of this disease, a clinically proven therapy is indicated.

Dosage

Unless otherwise prescribed, adults take 15-20 drops, 3 times per day. For pediatric dosages, consult your practitioner.

Warning

ASK DOCTOR

If symptoms persist, contact a licensed practitioner. If you have known sensitivity to any of the ingredients, please consult your licensed practitioner before use. If you are pregnant or nursing a baby, seek the advice of a health care professional before use.

Keep out of the reach of children.

STORAGE AND HANDLING

Protect from light and heat.

Tamper Evident

Do not use this product if tamper evident strip is broken or removed from base of cap.

QUESTIONS

To report adverse events, contact BioResource at 321B Blodgett Street, Cotati, CA 94931

Distributed by:
BioResource Inc.
Cotati, CA 94931

Manufactured by:
PEKANA® GmbH
D-88353 Kisslegg

PRINCIPAL DISPLAY PANEL - 50 ml Bottle Box

apo-ENTERIT™
Oral Drops

Homeopathic Medicine

For occasional
diarrhea and minor
stomach cramps

1.7 FL OZ
(50 ml)

PEKANA®